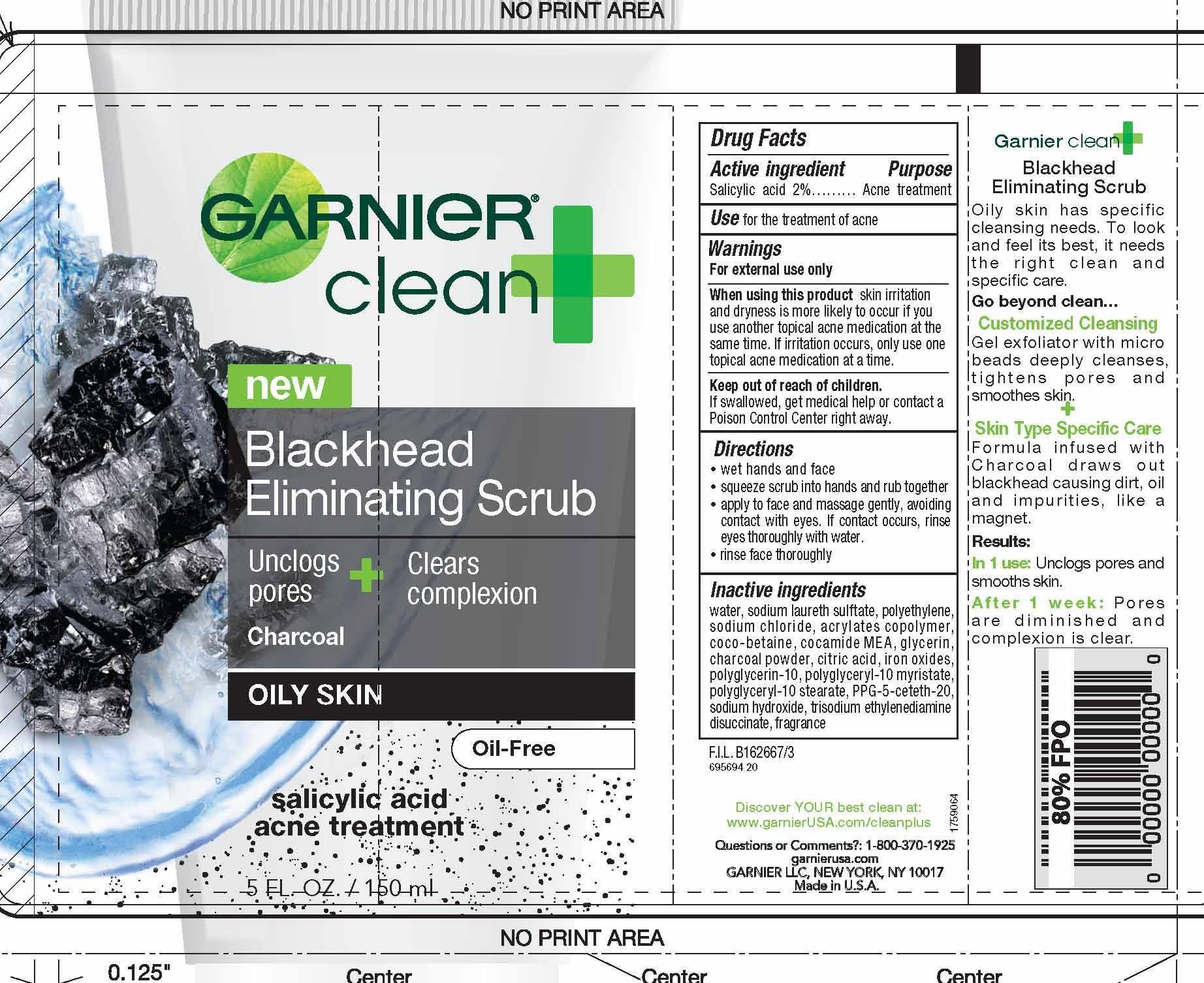 DRUG LABEL: Garnier Clean Blackhead Eliminating Scrub
NDC: 49967-035 | Form: GEL
Manufacturer: L'Oreal USA Products Inc
Category: otc | Type: HUMAN OTC DRUG LABEL
Date: 20240102

ACTIVE INGREDIENTS: SALICYLIC ACID 20 mg/1 mL
INACTIVE INGREDIENTS: WATER; SODIUM LAURETH SULFATE; HIGH DENSITY POLYETHYLENE; SODIUM CHLORIDE; BUTYL ACRYLATE/METHYL METHACRYLATE/METHACRYLIC ACID COPOLYMER (18000 MW); COCO-BETAINE; COCO MONOETHANOLAMIDE; GLYCERIN; ACTIVATED CHARCOAL; CITRIC ACID MONOHYDRATE; FERRIC OXIDE RED; POLYGLYCERIN-10; POLYGLYCERYL-2 MYRISTATE; POLYGLYCERYL-10 STEARATE; PPG-5-CETETH-20; SODIUM HYDROXIDE; TRISODIUM ETHYLENEDIAMINE DISUCCINATE

Drug Facts

Active ingredient

Salicylic acid 2%

Purpose

Acne treatment

Uses

for the treatment of acne

Warnings

For external use only

When using this product

skin irritation and dryness is more likely to occur if you use another topical acne medication at the same time. If irritation occurs, only use one topical acne medication at a time.

Keep out of reach of children.

If swallowed, get medical help or contact a Poison Control Center right away.

Directions

- wet hands and face

- squeeze scrub into hands and rub together

- apply to face and massage gently, avoiding contact with eyes. If contact occurs, rinse eyes thoroughy with water.

- rinse face thoroughly

Inactive ingredients

water, sodium laureth sulfate, polyethylene, sodium chloride, acrylates copolymer, coco-betaine, cocamide MEA, glycerin, charcoal powder, citric acid, iron oxides, polyglycerin-10, polyglyceryl-10 myristate, polyglyceryl-10 stearate, PPG-5-ceteth-20, sodium hydroxide, trisodium ethylenediamine, disuccinate, fragrance